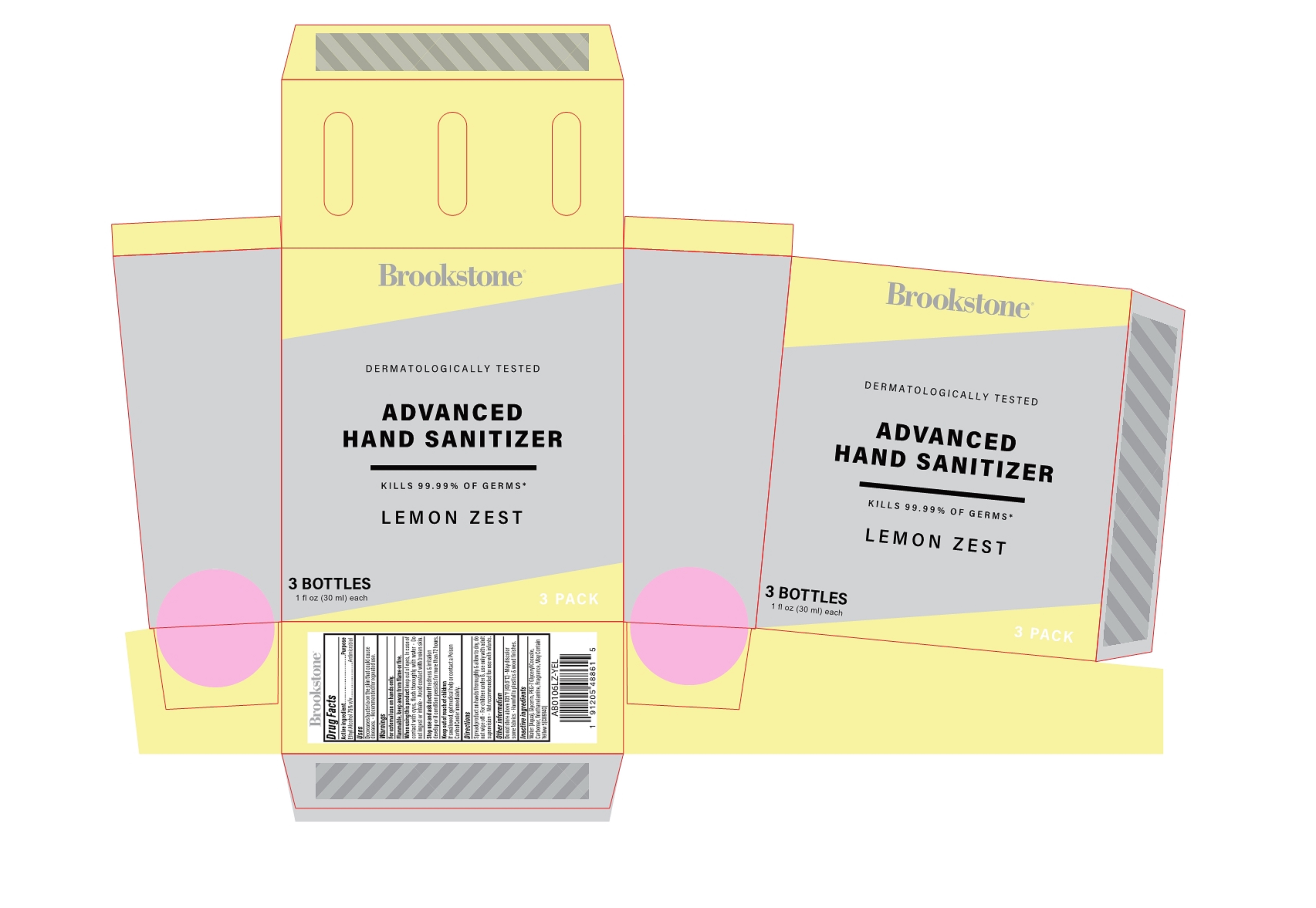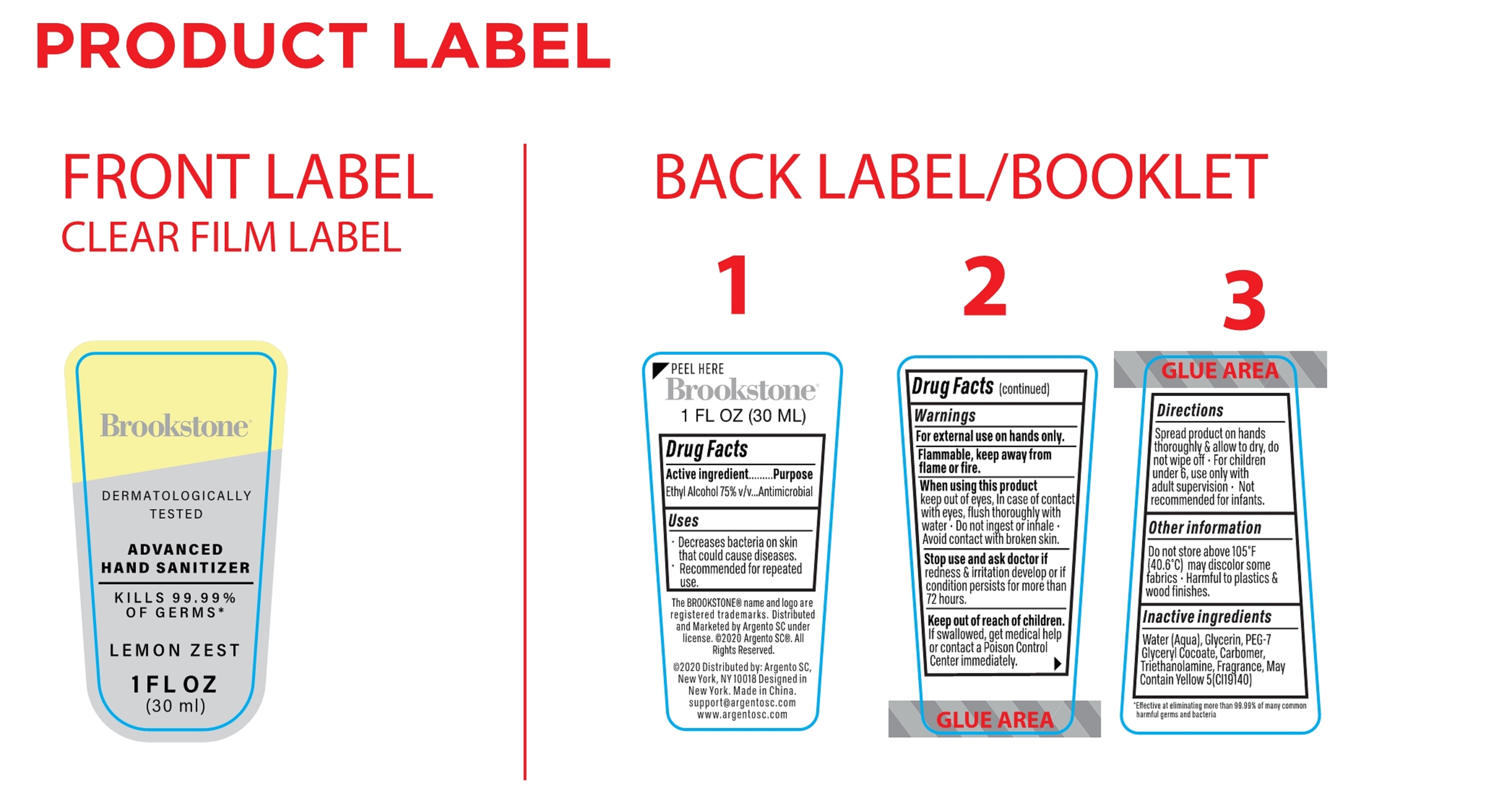 DRUG LABEL: BROOKSTONE ADVANCED HAND SANITIZER LEMON ZEST
NDC: 77731-302 | Form: GEL
Manufacturer: Argento sc by sicura inc.
Category: otc | Type: HUMAN OTC DRUG LABEL
Date: 20200908

ACTIVE INGREDIENTS: ALCOHOL 22.5 mL/30 mL
INACTIVE INGREDIENTS: GLYCERIN; PEG-7 GLYCERYL COCOATE; WATER; CARBOMER HOMOPOLYMER, UNSPECIFIED TYPE; FD&C YELLOW NO. 5; TROLAMINE; LEMON

77731-302 30ml BROOKSTONE ADVANCED HAND SANITIZER LEMON ZEST/ALCOHOL

Active Ingredient(s)

Ethyl Alcohol 75% v/v. Purpose: Antimicrobial

Purpose

Antimicrobial, Hand Sanitizer

Use

- Decreases bacteria on the skin that could cause diseases.
- Recommended for repeated use.

Warnings

- For external use on hand only.
- Flammable. Keep away from flame or fire.

Do not use

- in children less than 2 months of age
- on open skin wounds

- When using this product keep out of eyes, In case of contact with eyes, flush thoroughly with water.
- Do not ingest or inhale.
- Avoid contact with broken skin.

Stop use and ask a doctor if redness & irritation develop or if condition persists for more than 72 hours.

Keep out of reach of children. If swallowed, get medical help or contact a Poison Control Center immediately.

Directions

- Spread products on hands thoroughly & allow to dry, do not wipe off.
- For children under 6, use only with adult supervision.
- Not recommended for use with infants.

Other information

- Do not store above 105℉（40.6℃）.
- May discolor some fabrics.
- Harmfull to plastics & wood finishes.

Inactive ingredients

Aqua, Glycerin, PEG-7 GlycerylCocoate, Carbomer, Triethanolamine, Fragrance , May contain Yellow 5 (CI 19140).